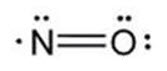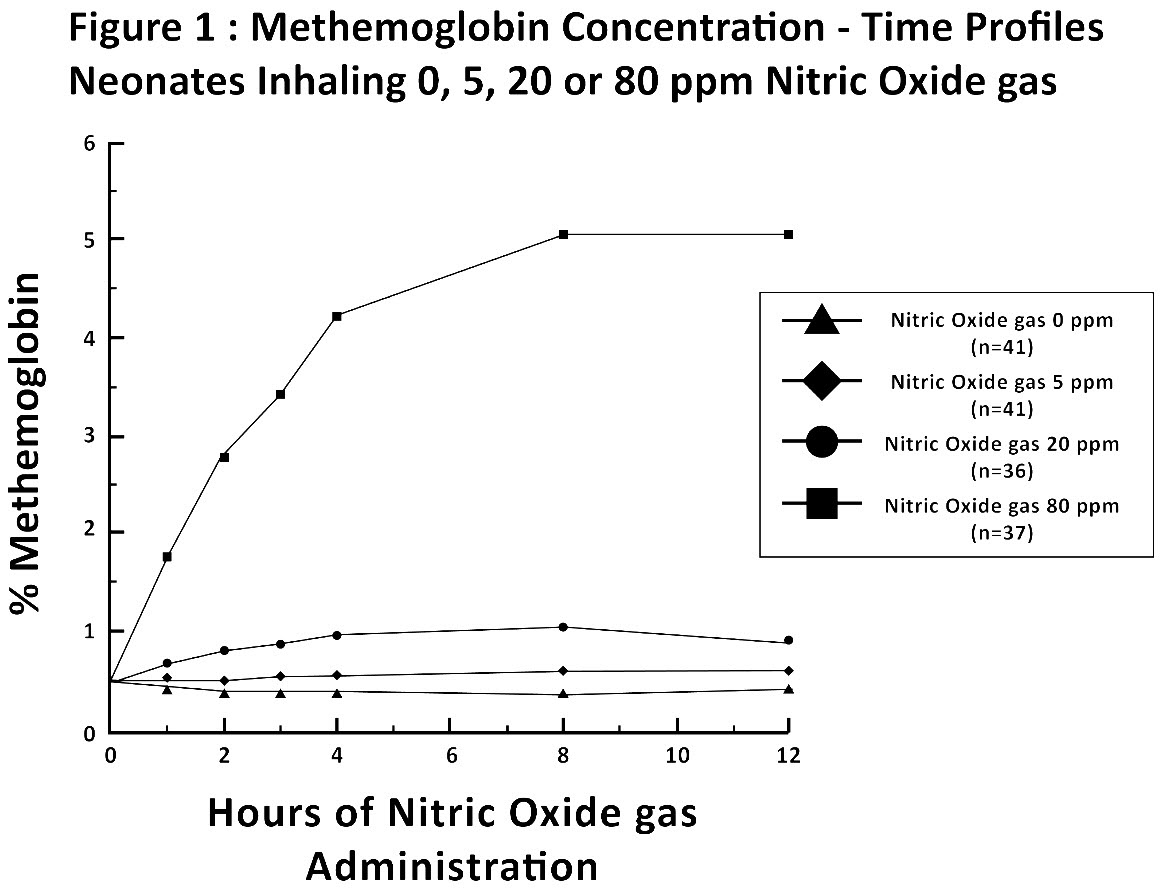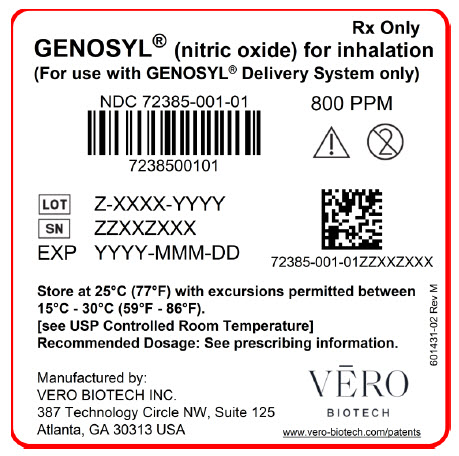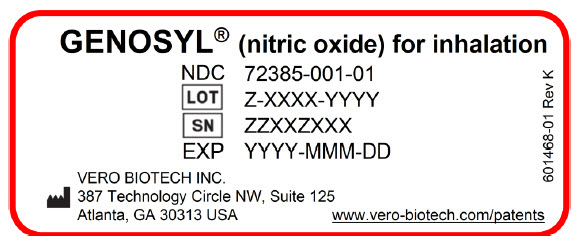 DRUG LABEL: GENOSYL
NDC: 72385-001 | Form: GAS
Manufacturer: VERO BIOTECH, INC.
Category: prescription | Type: HUMAN PRESCRIPTION DRUG LABEL
Date: 20251211

ACTIVE INGREDIENTS: NITRIC OXIDE 0.98 mg/1 L

HIGHLIGHTS OF PRESCRIBING INFORMATION

These highlights do not include all the information needed to use GENOSYL®safely and effectively. See full prescribing information for GENOSYL.GENOSYL (nitric oxide), for inhalation use
Initial U.S. Approval: 1999

1 INDICATIONS AND USAGE

GENOSYL®is a vasodilator indicated to improve oxygenation and reduce the need for extracorporeal membrane oxygenation in term and near-term (>34 weeks gestation) neonates with hypoxic respiratory failure associated with clinical or echocardiographic evidence of pulmonary hypertension in conjunction with ventilatory support and other appropriate agents (1).

2 DOSAGE AND ADMINISTRATION

The recommended dose is 20 ppm, maintained for up to 14 days or until the underlying oxygen desaturation has resolved (2.1).

Doses greater than 20 ppm are not recommended (2.1, 5.2).

Administration: Avoid abrupt discontinuation (2.2, 5.1).

3 DOSAGE FORMS AND STRENGTHS

GENOSYL (nitric oxide) is a gas, available at concentrations up to 800 ppm.

4 CONTRAINDICATIONS

Neonates dependent on right-to-left shunting of blood (4).

5 WARNINGS AND PRECAUTIONS

Rebound Pulmonary Hypertension: Abrupt discontinuation of GENOSYL may lead to worsening oxygenation and increasing pulmonary artery pressure (5.1).

Methemoglobinemia: Methemoglobin increases with the dose of nitric oxide; following discontinuation or reduction of nitric oxide, methemoglobin levels return to baseline over a period of hours (5.2).

Elevated NO2Levels: Monitor NO2levels (5.3).

Heart Failure: In patients with pre-existing left ventricular dysfunction, GENOSYL may increase pulmonary capillary wedge pressure leading to pulmonary edema (5.4).

6 ADVERSE REACTIONS

The most common adverse reaction is hypotension (6).

To report SUSPECTED ADVERSE REACTIONS, contact Vero Biotech at 1-877-337-4118 and http://www.vero-biotech.com/ or FDA at 1-800-FDA-1088 orwww.fda.gov/medwatch.

7 DRUG INTERACTIONS

Nitric oxide donor compounds may increase the risk of developing methemoglobinemia (7).

FULL PRESCRIBING INFORMATION

1 INDICATIONS AND USAGE

GENOSYL®is indicated to improve oxygenation and reduce the need for extracorporeal membrane oxygenation in term and near-term (>34 weeks gestation) neonates with hypoxic respiratory failure associated with clinical or echocardiographic evidence of pulmonary hypertension in conjunction with ventilatory support and other appropriate agents.

2 DOSAGE AND ADMINISTRATION

2.1 Dosage

Term and near-term neonates withhypoxic respiratory failure

The recommended dose of GENOSYL is 20 ppm. Maintain treatment up to 14 days or until the underlying oxygen desaturation has resolved and the neonate is ready to be weaned from GENOSYL therapy.

Doses greater than 20 ppm are not recommended [see Warnings and Precautions (5.2)].

2.2 Administration

Nitric Oxide Delivery System

GENOSYL must be administered using a calibrated GENOSYL Delivery System. Only validated ventilator systems should be used in conjunction with GENOSYL [see Description (11)].

Consult the GENOSYL Delivery System Operator's Manual or call 1-877-337-4118 or visit www.vero-biotech.comfor needed information on training and technical support for users of GENOSYL with the GENOSYL Delivery System .

Keep available a backup power supply to address power failures. The GENOSYL Delivery System consists of a primary system and a fully functional second system that can be used as backup in the event of primary system failure.

Monitoring

Measure methemoglobin within 4-8 hours after initiation of treatment with GENOSYL and periodically throughout treatment [see Warnings and Precautions (5.2)].

Monitor for PaO2and inspired NO2during GENOSYL administration [see Warnings and Precautions (5.3)].

The concentration of nitric oxide, nitrogen dioxide and air is constantly monitored. The GENOSYL Delivery System will shutdown if nitrogen dioxide reaches 3 ppm.

Weaning and Discontinuation

Avoid abrupt discontinuation of GENOSYL [see Warnings and Precautions (5.1)]. To wean GENOSYL, down titrate in several steps, pausing several hours at each step to monitor for hypoxemia.

3 DOSAGE FORMS AND STRENGTHS

GENOSYL (nitric oxide) is a gas available at concentrations up to 800 ppm [see Description (11)] .

4 CONTRAINDICATIONS

GENOSYL is contraindicated in neonates dependent on right-to-left shunting of blood.

5 WARNINGS AND PRECAUTIONS

5.1 Rebound Pulmonary Hypertension Syndrome following Abrupt Discontinuation

Wean from GENOSYL [see Dosage and Administration (2.2)]. Abrupt discontinuation of GENOSYL may lead to worsening oxygenation and increasing pulmonary artery pressure, i.e., Rebound Pulmonary Hypertension Syndrome. Signs and symptoms of Rebound Pulmonary Hypertension Syndrome include hypoxemia, systemic hypotension, bradycardia, and decreased cardiac output. If Rebound Pulmonary Hypertension occurs, reinstate GENOSYL therapy immediately.

5.2 Hypoxemia from Methemoglobinemia

Nitric oxide combines with hemoglobin to form methemoglobin, which does not transport oxygen. Methemoglobin levels increase with the dose of GENOSYL; it can take 8 hours or more before steady-state methemoglobin levels are attained. Monitor methemoglobin and adjust the dose of GENOSYL to optimize oxygenation.

If methemoglobin levels do not resolve with decrease in dose or discontinuation of GENOSYL, additional therapy may be warranted to treat methemoglobinemia [see Overdosage (10)] .

5.3 Airway Injury from Nitrogen Dioxide

Nitrogen dioxide (NO2) forms in gas mixtures containing NO and O2. Nitrogen dioxide may cause airway inflammation and damage to lung tissues.

If there is an unexpected change in NO2concentration, or if the NO2concentration reaches 0.5 ppm when measured in the breathing circuit, then the delivery system should be assessed in accordance with the GENOSYL Delivery System Operator's Manual troubleshooting section, and the NO2analyzer should be recalibrated. The dose of GENOSYL and/or FiO2should be adjusted as appropriate.

5.4 Worsening Heart Failure

Patients with left ventricular dysfunction treated with GENOSYL may experience pulmonary edema, increased pulmonary capillary wedge pressure, worsening of left ventricular dysfunction, systemic hypotension, bradycardia and cardiac arrest. Discontinue GENOSYL while providing symptomatic care.

6 ADVERSE REACTIONS

The following adverse reactions are discussed elsewhere in the label;

Hypoxemia [see Warnings and Precautions (5.2)]

Worsening Heart Failure [see Warnings and Precautions (5.4)]

6.1 Clinical Trials Experience

Because clinical trials are conducted under widely varying conditions, adverse reaction rates observed in the clinical trials of a drug cannot be directly compared to rates in the clinical trials of another drug and may not reflect the rates observed in practice. The adverse reaction information from the clinical studies does, however, provide a basis for identifying the adverse events that appear to be related to drug use and for approximating rates.

Controlled studies have included 325 patients on nitric oxide doses of 5 to 80 ppm and 251 patients on placebo. Total mortality in the pooled trials was 11% on placebo and 9% on nitric oxide gas for inhalation, a result adequate to exclude nitric oxide mortality being more than 40% worse than placebo.

In both the NINOS and CINRGI studies, the duration of hospitalization was similar in nitric oxide gas for inhalation and placebo-treated groups.

From all controlled studies, at least 6 months of follow-up is available for 278 patients who received nitric oxide gas and 212 patients who received placebo. Among these patients, there was no evidence of an adverse effect of treatment on the need for re-hospitalization, special medical services, pulmonary disease, and neurological sequelae.

In the NINOS study, treatment groups were similar with respect to the incidence and severity of intracranial hemorrhage, Grade IV hemorrhage, periventricular leukomalacia, cerebral infarction, seizures requiring anticonvulsant therapy, pulmonary hemorrhage, or gastrointestinal hemorrhage.

In CINRGI, the only adverse reaction (>2% higher incidence on nitric oxide gas for inhalation than on placebo) was hypotension (14% vs. 11%).

6.2 Postmarketing Experience

Post marketing reports of accidental exposure to nitric oxide for inhalation in hospital staff has been associated with chest discomfort, dizziness, dry throat, dyspnea, and headache.

7 DRUG INTERACTIONS

7.1 Nitric Oxide Donor Agents

Nitric oxide donor agents such as prilocaine, sodium nitroprusside and nitroglycerine may increase the risk of developing methemoglobinemia.

8 USE IN SPECIFIC POPULATIONS

8.4 Pediatric Use

The safety and efficacy of nitric oxide for inhalation has been demonstrated in term and near-term neonates with hypoxic respiratory failure associated with evidence of pulmonary hypertension [see Clinical Studies (14.1)] . Additional studies conducted in premature neonates for the prevention of bronchopulmonary dysplasia have not demonstrated substantial evidence of efficacy [see Clinical Studies (14.3)] . No information about its effectiveness in other age populations is available.

8.5 Geriatric Use

Nitric oxide is not indicated for use in the adult population.

10 OVERDOSAGE

Overdosage with nitric oxide gas is manifest by elevations in methemoglobin and pulmonary toxicities associated with inspired NO2. Elevated NO2may cause acute lung injury. Elevations in methemoglobin reduce the oxygen delivery capacity of the circulation. In clinical studies, NO2levels >3 ppm or methemoglobin levels >7% were treated by reducing the dose of, or discontinuing, nitric oxide gas.

Methemoglobinemia that does not resolve after reduction or discontinuation of therapy can be treated with intravenous vitamin C, intravenous methylene blue, or blood transfusion, based upon the clinical situation.

11 DESCRIPTION

GENOSYL (nitric oxide) is administered by inhalation. Nitric oxide is a pulmonary vasodilator. Nitric oxide is generated from liquid dinitrogen tetroxide (N2O4) by the cassette in the GENOSYL Delivery System. Upon initiation of GENOSYL Delivery System, the liquid N2O4is heated and the equilibrium shifts to nitrogen dioxide (NO2) gas. The NO2is then converted into nitric oxide (NO) using the antioxidant cartridges, and nitric oxide is delivered to the patient by means of a ventilator or a nasal cannula. The amount of nitric oxide administered to the patient is set by controlling the temperature of the N2O4liquid module, which controls the pressure inside the liquid module, which in turn controls the mass of NO2that is sent to the primary cartridges, and hence the mass of nitric oxide. The mass flow of nitric oxide, together with the air from the pump, control the nitric oxide concentration. A nitric oxide sensor monitors the nitric oxide in the patient line. GENOSYL Delivery System is designed to deliver a controlled level of nitric oxide blended with breathing air or oxygen-enriched breathing air.

The GENOSYL Delivery System controls the flow of nitric oxide mixed with air delivered to the patient.

The structural formula of nitric oxide (NO) is shown below:

12 CLINICAL PHARMACOLOGY

12.1 Mechanism of Action

Nitric oxide relaxes vascular smooth muscle by binding to the heme moiety of cytosolic guanylate cyclase, activating guanylate cyclase and increasing intracellular levels of cyclic guanosine 3',5'-monophosphate, which then leads to vasodilation. When inhaled, nitric oxide selectively dilates the pulmonary vasculature, and because of efficient scavenging by hemoglobin, has minimal effect on the systemic vasculature.

GENOSYL appears to increase the partial pressure of arterial oxygen (PaO2) by dilating pulmonary vessels in better ventilated areas of the lung, redistributing pulmonary blood flow away from lung regions with low ventilation/perfusion (V/Q) ratios toward regions with normal ratios.

12.2 Pharmacodynamics

Effects on Pulmonary Vascular Tone in PPHN

Persistent pulmonary hypertension of the newborn (PPHN) occurs as a primary developmental defect or as a condition secondary to other diseases such as meconium aspiration syndrome (MAS), pneumonia, sepsis, hyaline membrane disease, congenital diaphragmatic hernia (CDH), and pulmonary hypoplasia. In these states, pulmonary vascular resistance (PVR) is high, which results in hypoxemia secondary to right-to-left shunting of blood through the patent ductus arteriosus and foramen ovale. In neonates with PPHN, nitric oxide gas for inhalation improves oxygenation (as indicated by significant increases in PaO2).

12.3 Pharmacokinetics

The pharmacokinetics of nitric oxide has been studied in adults.

Absorption and Distribution

Nitric oxide is absorbed systemically after inhalation. Most of it traverses the pulmonary capillary bed where it combines with hemoglobin that is 60% to 100% oxygen-saturated. At this level of oxygen saturation, nitric oxide combines predominantly with oxyhemoglobin to produce methemoglobin and nitrate. At low oxygen saturation, nitric oxide can combine with deoxyhemoglobin to transiently form nitrosylhemoglobin, which is converted to nitrogen oxides and methemoglobin upon exposure to oxygen. Within the pulmonary system, nitric oxide can combine with oxygen and water to produce nitrogen dioxide and nitrite, respectively, which interact with oxyhemoglobin to produce methemoglobin and nitrate. Thus, the end products of nitric oxide that enter the systemic circulation are predominantly methemoglobin and nitrate.

Metabolism

Methemoglobin disposition has been investigated as a function of time and nitric oxide exposure concentration in neonates with respiratory failure. The methemoglobin (MetHb) concentration-time profiles during the first 12 hours of exposure to 0, 5, 20, and 80 ppm nitric oxide are shown in Figure 1.

Methemoglobin concentrations increased during the first 8 hours of nitric oxide exposure. The mean methemoglobin level remained below 1% in the placebo group and in the 5 ppm and 20 ppm nitric oxide gas groups, but reached approximately 5% in the 80 ppm nitric oxide gas group. Methemoglobin levels >7% were attained only in patients receiving 80 ppm, where they comprised 35% of the group. The average time to reach peak methemoglobin was 10 ± 9 (SD) hours (median, 8 hours) in these 13 patients, but one patient did not exceed 7% until 40 hours.

Elimination

Nitrate has been identified as the predominant nitric oxide metabolite excreted in the urine, accounting for >70% of the nitric oxide dose inhaled. Nitrate is cleared from the plasma by the kidney at rates approaching the rate of glomerular filtration.

13 NONCLINICAL TOXICOLOGY

13.1 Carcinogenesis, Mutagenesis, Impairment of Fertility

No evidence of a carcinogenic effect was apparent, at inhalation exposures up to the recommended dose (20 ppm), in rats for 20 hr/day for up to two years. Higher exposures have not been investigated.

Nitric oxide gas has demonstrated genotoxicity in Salmonella (Ames Test), human lymphocytes, and after in vivo exposure in rats. There are no animal or human studies to evaluate nitric oxide for effects on fertility.

14 CLINICAL STUDIES

14.1 Treatment of Hypoxic Respiratory Failure (HRF)

The efficacy of nitric oxide gas was investigated in term and near-term newborns with hypoxic respiratory failure (HRF) resulting from a variety of etiologies. Inhalation of nitric oxide gas reduces the oxygenation index (OI= mean airway pressure in cm H2O × fraction of inspired oxygen concentration [FiO2]× 100 divided by systemic arterial concentration in mm Hg [PaO2]) and increases PaO2 [see Clinical Pharmacology (12.1)] .

NINOS Study

The Neonatal Inhaled Nitric Oxide Study (NINOS) was a double-blind, randomized, placebo-controlled, multicenter trial in 235 neonates with hypoxic respiratory failure. The objective of the study was to determine whether inhaled nitric oxide would reduce the occurrence of death and/or initiation of extracorporeal membrane oxygenation (ECMO) in a prospectively defined cohort of term or near-term neonates with hypoxic respiratory failure unresponsive to conventional therapy. Hypoxic respiratory failure was caused by meconium aspiration syndrome (MAS; 49%), pneumonia/sepsis (21%), idiopathic primary pulmonary hypertension of the newborn (PPHN; 17%), or respiratory distress syndrome (RDS; 11%). Infants 14 days of age (mean, 1.7 days) with a mean PaO2of 46 mm Hg and a mean oxygenation index (OI) of 43 cm H2O / mm Hg were initially randomized to receive 100% O2with (n=114) or without (n=121) 20 ppm nitric oxide for up to 14 days. Response to study drug was defined as a change from baseline in PaO230 minutes after starting treatment (full response = >20 mm Hg, partial = 10-20 mm Hg, no response = <10 mm Hg). Neonates with a less than full response were evaluated for a response to 80 ppm nitric oxide or control gas. The primary results of this study are presented in Table 1.

Table 1: Summary of Clinical Results from Hypoxic Respiratory Failure Study
 | Control (n=121) | Nitric Oxide gas (n=114) | P value
Death or ECMO [Death or need for ECMO was the primary end point of this study] [Extracorporeal membrane oxygenation] | 77 (64%) | 52 (46%) | 0.006
Death | 20 (17%) | 16 (14%) | 0.60
ECMO | 66 (55%) | 44 (39%) | 0.014

Although the incidence of death by 120 days of age was similar in both groups (NO, 14%; control 17%), significantly fewer infants in the nitric oxide group required ECMO compared with controls (39% vs. 55%, p = 0.014). The combined incidence of death and/or initiation of ECMO showed a significant advantage for the nitric oxide treated group (46% vs. 64%, p = 0.006). The nitric oxide group also had significantly greater increases in PaO2and greater decreases in the OI and the alveolar-arterial oxygen gradient than the control group (p<0.001 for all parameters). Significantly more patients had at least a partial response to the initial administration of study drug in the nitric oxide group (66%) than the control group (26%, p<0.001). Of the 125 infants who did not respond to 20 ppm nitric oxide control, similar percentages of NO-treated (18%) and control (20%) patients had at least a partial response to 80 ppm nitric oxide gas for inhalation or control drug, suggesting a lack of additional benefit for the higher dose of nitric oxide. No infant had study drug discontinued for toxicity. Inhaled nitric oxide gas had no detectable effect on mortality. The adverse events collected in the NINOS trial occurred at similar incidence rates in both treatment groups [see Adverse Reactions (6.1)] . Follow-up exams were performed at 18-24 months for the infants enrolled in this trial. In the infants with available follow-up, the two treatment groups were similar with respect to their mental, motor, audiologic, or neurologic evaluations.

CINRGI Study

This study was a double-blind, randomized, placebo-controlled, multi-center trial of 186 term and near-term neonates with pulmonary hypertension and hypoxic respiratory failure. The primary objective of the study was to determine whether nitric oxide gas would reduce the receipt of ECMO in these patients. Hypoxic respiratory failure was caused by MAS (35%), idiopathic PPHN (30%), pneumonia/sepsis (24%), or RDS (8%). Patients with a mean PaO2of 54 mm Hg and a mean OI of 44 cm H2O / mm Hg were randomly assigned to receive either 20 ppm nitric oxide gas (n=97) or nitrogen gas (placebo; n=89) in addition to their ventilatory support. Patients who exhibited a PaO2>60 mm Hg and a pH < 7.55 were weaned to 5 ppm nitric oxide gas or placebo. The primary results from the CINRGI study are presented in Table 2.

Table 2: Summary of Clinical Results from Persistent Pulmonary Hypertension of the Newborn Study
 | Placebo | Nitric oxide gas | P value
ECMO [ECMO was the primary end point of this study] [Extracorporeal membrane oxygenation] | 51/89 (57%) | 30/97 (31%) | <0.001
Death | 5/89 (6%) | 3/97 (3%) | 0.48

Significantly fewer neonates in the nitric oxide gas group required ECMO compared to the control group (31% vs. 57%, p<0.001). While the number of deaths were similar in both groups (Nitric oxide gas, 3%; placebo, 6%), the combined incidence of death and/or receipt of ECMO was decreased in the nitric oxide gas group (33% vs. 58%, p<0.001).

In addition, the nitric oxide gas group had significantly improved oxygenation as measured by PaO2, OI, and alveolar-arterial gradient (p<0.001 for all parameters). Of the 97 patients treated with nitric oxide gas, 2 (2%) were withdrawn from study drug due to methemoglobin levels >4%. The frequency and number of adverse events reported were similar in the two study groups [see Adverse Reactions (6.1)] .

In clinical trials, reduction in the need for ECMO has not been demonstrated with the use of inhaled nitric oxide in neonates with congenital diaphragmatic hernia (CDH).

14.2 Ineffective in Adult Respiratory Distress Syndrome (ARDS)

In a randomized, double-blind, parallel, multicenter study, 385 patients with adult respiratory distress syndrome (ARDS) associated with pneumonia (46%), surgery (33%), multiple trauma (26%), aspiration (23%), pulmonary contusion (18%), and other causes, with PaO2/FiO2<250 mm Hg despite optimal oxygenation and ventilation, received placebo (n=193) or nitric oxide gas (n=192), 5 ppm, for 4 hours to 28 days or until weaned because of improvements in oxygenation. Despite acute improvements in oxygenation, there was no effect of nitric oxide gas on the primary endpoint of days alive and off ventilator support. These results were consistent with outcome data from a smaller dose ranging study of nitric oxide (1.25 to 80 ppm). GENOSYL (nitric oxide) for inhalation is not indicated for use in ARDS.

14.3 Ineffective in Prevention of Bronchopulmonary Dysplasia (BPD)

The safety and efficacy of nitric oxide gas for the prevention of chronic lung disease [bronchopulmonary dysplasia (BPD)] in neonates ≤ 34 weeks gestational age requiring respiratory support has been studied in four large previously conducted multicenter, double-blind, placebo-controlled clinical trials in a total of 2,600 preterm infants. Of these, 1,290 received placebo, and 1,310 received inhaled nitric oxide at doses ranging from 5-20 ppm, for treatment periods of 7-24 days duration. The primary endpoint for these studies was alive and without BPD at 36 weeks postmenstrual age (PMA). The need for supplemental oxygen at 36 weeks PMA served as a surrogate endpoint for the presence of BPD. Overall, efficacy for the prevention of bronchopulmonary dysplasia in preterm infants was not established. There were no meaningful differences between treatment groups with regard to overall deaths, methemoglobin levels, or adverse events commonly observed in premature infants, including intraventricular hemorrhage, patent ductus arteriosus, pulmonary hemorrhage, and retinopathy of prematurity.

The use of GENOSYL (nitric oxide) for prevention of BPD in preterm neonates ≤34 weeks gestational age is not recommended.

16 HOW SUPPLIED/STORAGE AND HANDLING

GENOSYL Delivery System cassettes produce at least 216 liters of 800 ppm nitric oxide gas (at standard temperature and pressure, STP) (NDC 72385-001-01).

STORAGE AND HANDLING

Store at 20°C to 25°C (68°F to 77°F) with excursions permitted between 15°C –30°C (59°F –86°F) [see USP Controlled Room Temperature].

The GENOSYL Delivery System must be used with antioxidant cartridges not older than 12 months from the manufacturing date.

Occupational Exposure

The exposure limit set by the Occupational Safety and Health Administration (OSHA) for nitric oxide is 25 ppm, and for NO2the limit is 5ppm.

Rx Only

GENOSYL is a registered trademark of Vero Biotech.

©2019 Vero Biotech

Manufactured by:
VERO BIOTECH
387 Technology Circle NW
Suite 125
Atlanta, GA 30313, USA
[601531]

PRINCIPAL DISPLAY PANEL - 216 L Cartridge Label - Cassette Front

Rx Only

GENOSYL®(nitric oxide) for inhalation
(For use with GENOSYL®Delivery System only)

NDC 72385-001-01
800 PPM

LOT Z-XXXX-YYYY

SN ZZXXZXXX

EXP YYYY-MMM-DD

72385-001-01ZZXXZXXX

Store at 25°C (77°F) with excursions permitted between
15°C - 30°C (59°F - 86°F).
[see USP Controlled Room Temperature]
Recommended Dosage: See prescribing information.

Manufactured by:
VERO BIOTECH INC.
387 Technology Circle NW, Suite 125
Atlanta, GA 30313 USA

VĒRO
BIOTECH

www.vero-biotech.com/patents

601431-02 Rev M

PRINCIPAL DISPLAY PANEL - 216 L Cartridge Label - Cassette Top

GENOSYL®(nitric oxide) for inhalation

NDC 72385-001-01

LOT Z-XXXX-YYYY

SN ZZXXZXXX

EXP YYYY-MMM-DD

VERO BIOTECH INC.
387 Technology Circle NW, Suite 125
Atlanta, GA 30313 USA

www.vero-biotech.com/patents

601468-01 Rev K